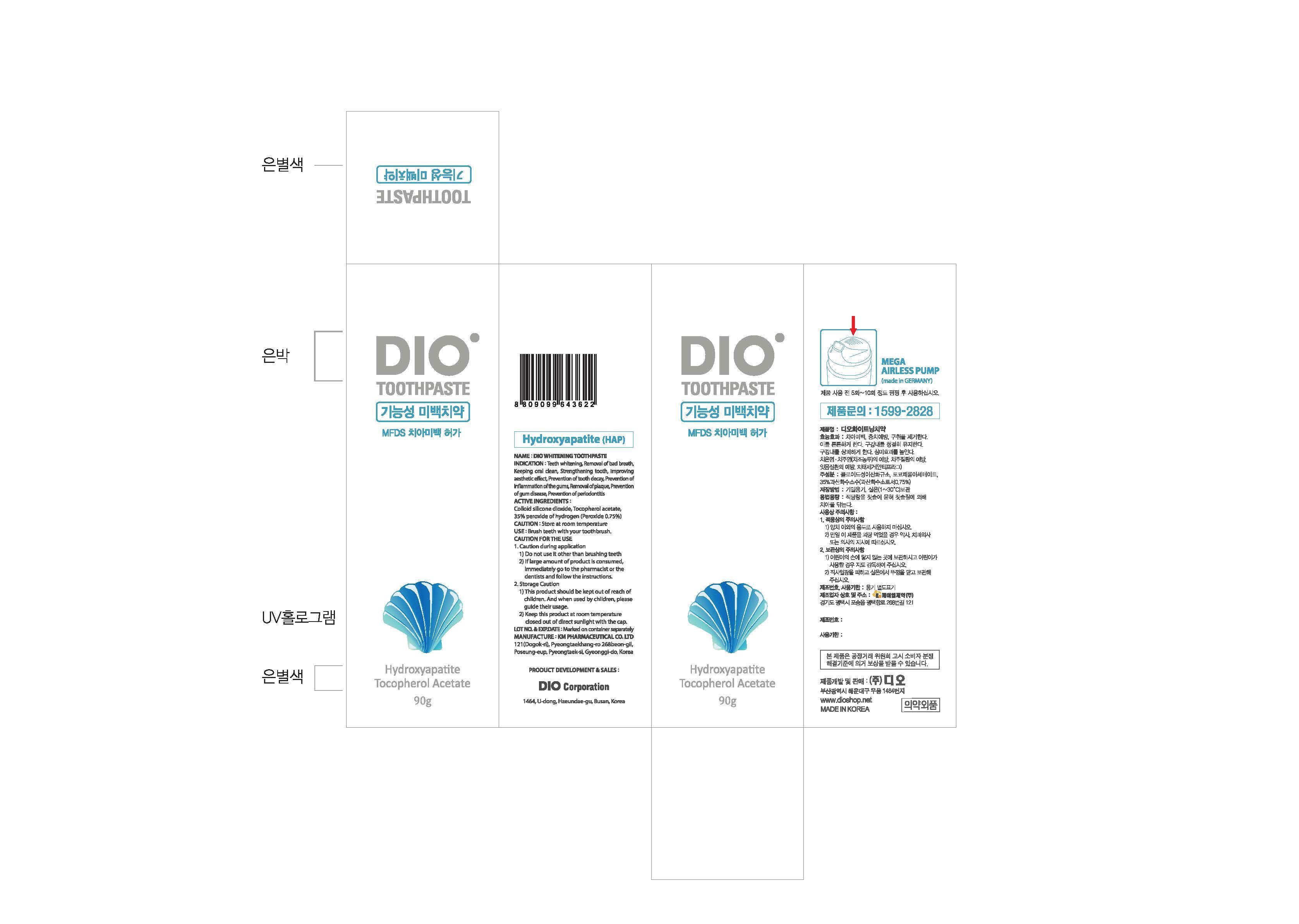 DRUG LABEL: DIO WHITENING
NDC: 75902-4001 | Form: PASTE, DENTIFRICE
Manufacturer: Dio Corporation
Category: otc | Type: HUMAN OTC DRUG LABEL
Date: 20170601

ACTIVE INGREDIENTS: SILICON DIOXIDE 7 g/100 g; .ALPHA.-TOCOPHEROL ACETATE 0.2 g/100 g; HYDROGEN PEROXIDE 2.14 g/100 g
INACTIVE INGREDIENTS: XYLITOL; WATER

Drug Facts

ACTIVE INGREDIENT

colloidal silicon dioxide, tocopherol acetate, 35% hydrogen peroxide solution

INACTIVE INGREDIENT

xylityl, sorbitol solution 70%, polyethylene glycol 1500, carboxymethylcellulose sodium, xanthan gum, poly vinyl pirrolidone, sodium stannate, etc.

PURPOSE

for dental care

keep out of reach of the children

INDICATIONS AND USAGE

brush teeth with your toothbrush

WARNINGS

store at room temperature

DOSAGE AND ADMINISTRATION

for dental use only